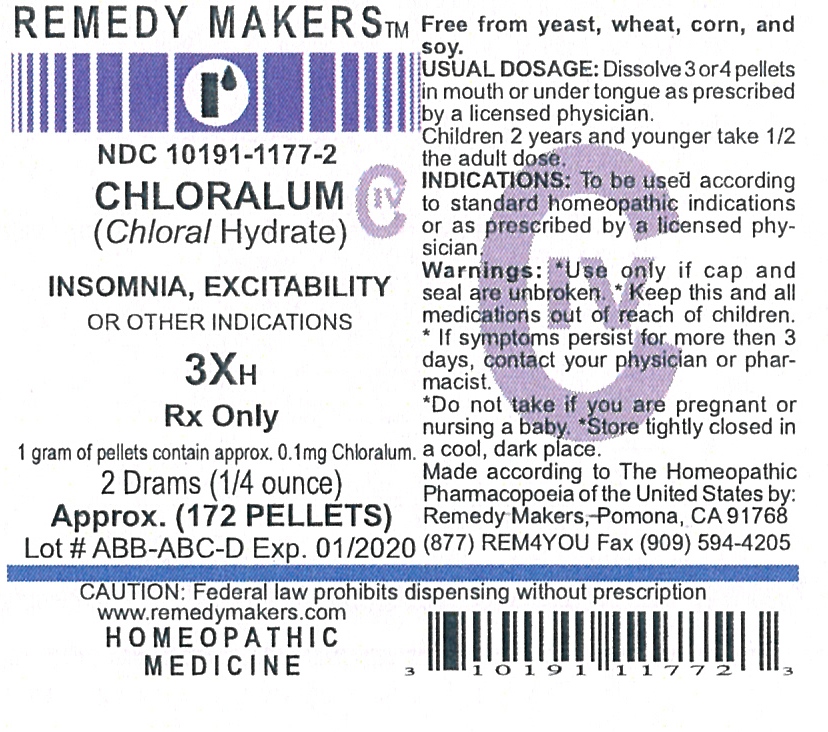 DRUG LABEL: CHLORALUM
NDC: 10191-1177 | Form: PELLET
Manufacturer: Remedy Makers
Category: homeopathic | Type: HUMAN PRESCRIPTION DRUG LABEL
Date: 20110307
DEA Schedule: CIV

ACTIVE INGREDIENTS: CHLORAL HYDRATE 3 [hp_X]/1 1
INACTIVE INGREDIENTS: SUCROSE; LACTOSE

CHLORALUM 3X (Chloral Hydrate)

CONTROLLED SUBSTANCE

Chloral Hydrate

PURPOSE

INSOMNIA, EXCITABILITY, OR OTHER INDICATIONS

KEEP OUT OF REACH OF CHILDREN

WARNING: Keep this and all medications out of reach of children.

INDICATIONS AND USAGE

INDICATIONS: To be used according to standard homeopathic indications for self limiting conditions such as those indicated on the front panel or as directed by a physician.

Free from yeast, wheat, corn, and soy.

WARNINGS

WARNING: Used only if cap and seal are unbroken. If symptoms persist for more then 3 days, consult your physician. As with any drug, if your pregnant or nursing a baby, seek the advise of a health professional before using this product. Store tightly closed in a cool, dark place. Made according to The Homeopathic Pharmacopoeia of the United State by: Remedy Makers, Pomona, CA 91768.

DOSAGE AND ADMINISTRATION

DIRECTION: Dissolve 3 or 4 in mouth or tongue 3 times a day or as directed by a physician. Children 2 years and older take 1/2 adult dose.

INACTIVE INGREDIENT

80% SUCROSE / 20% LACTOSE